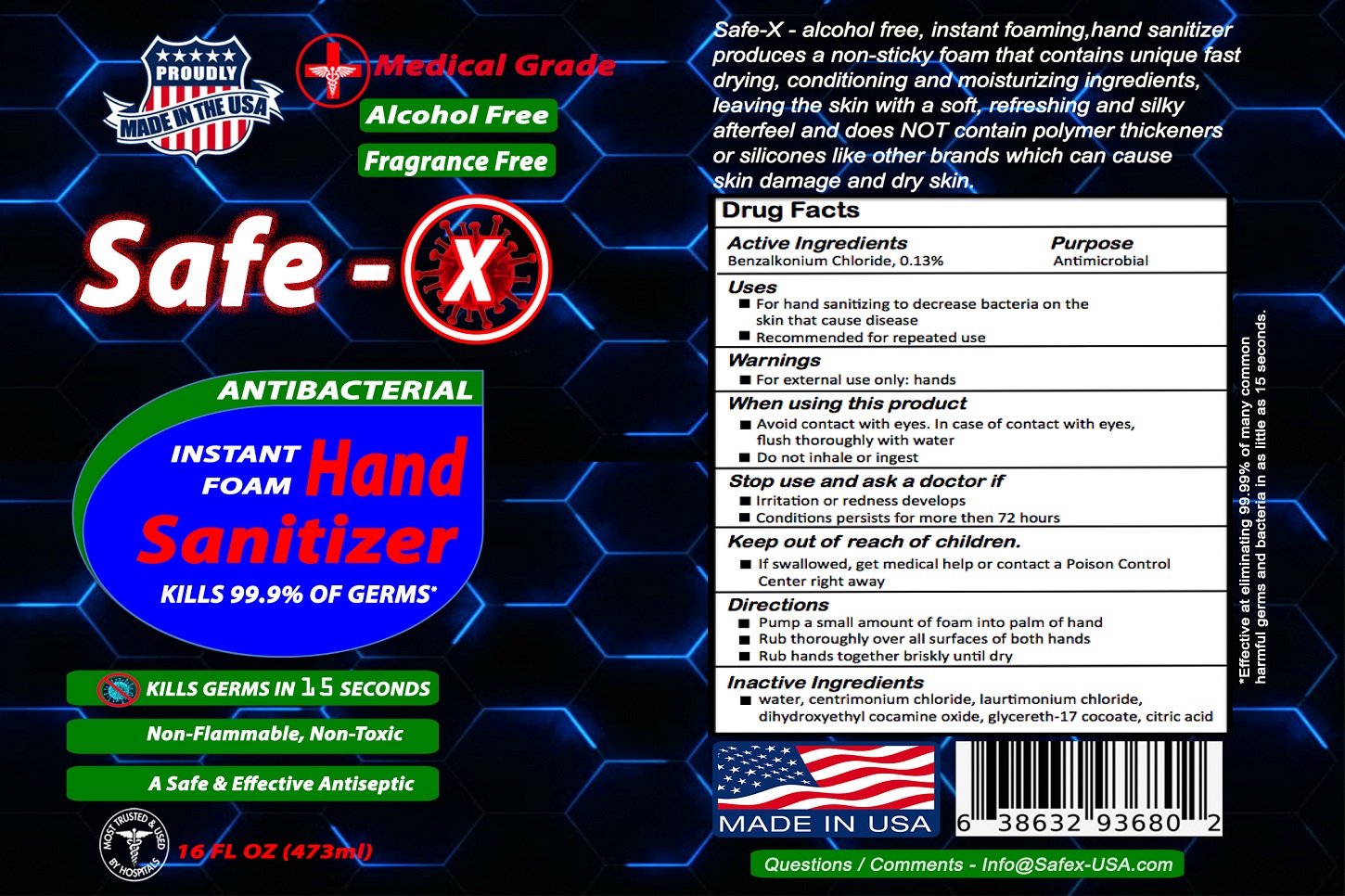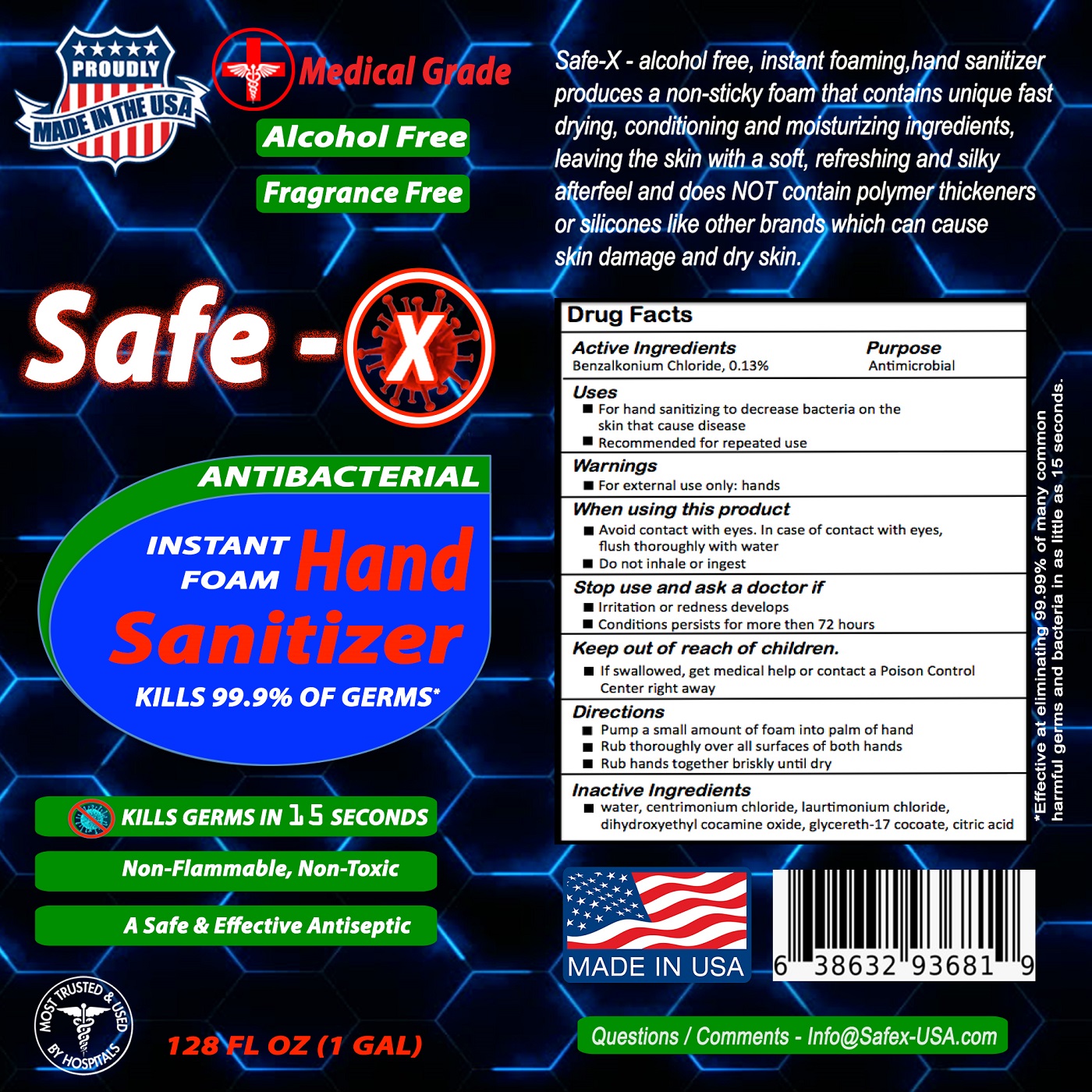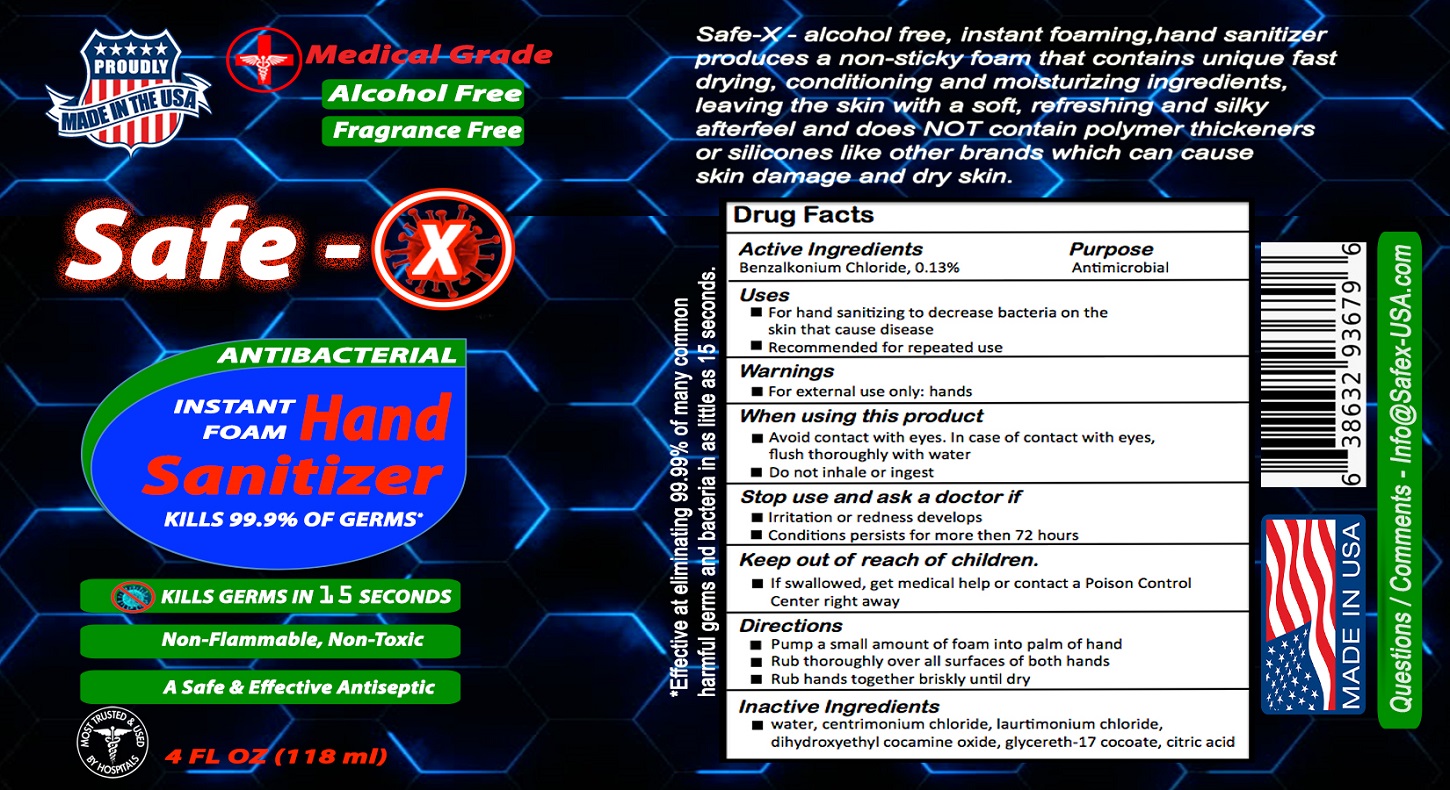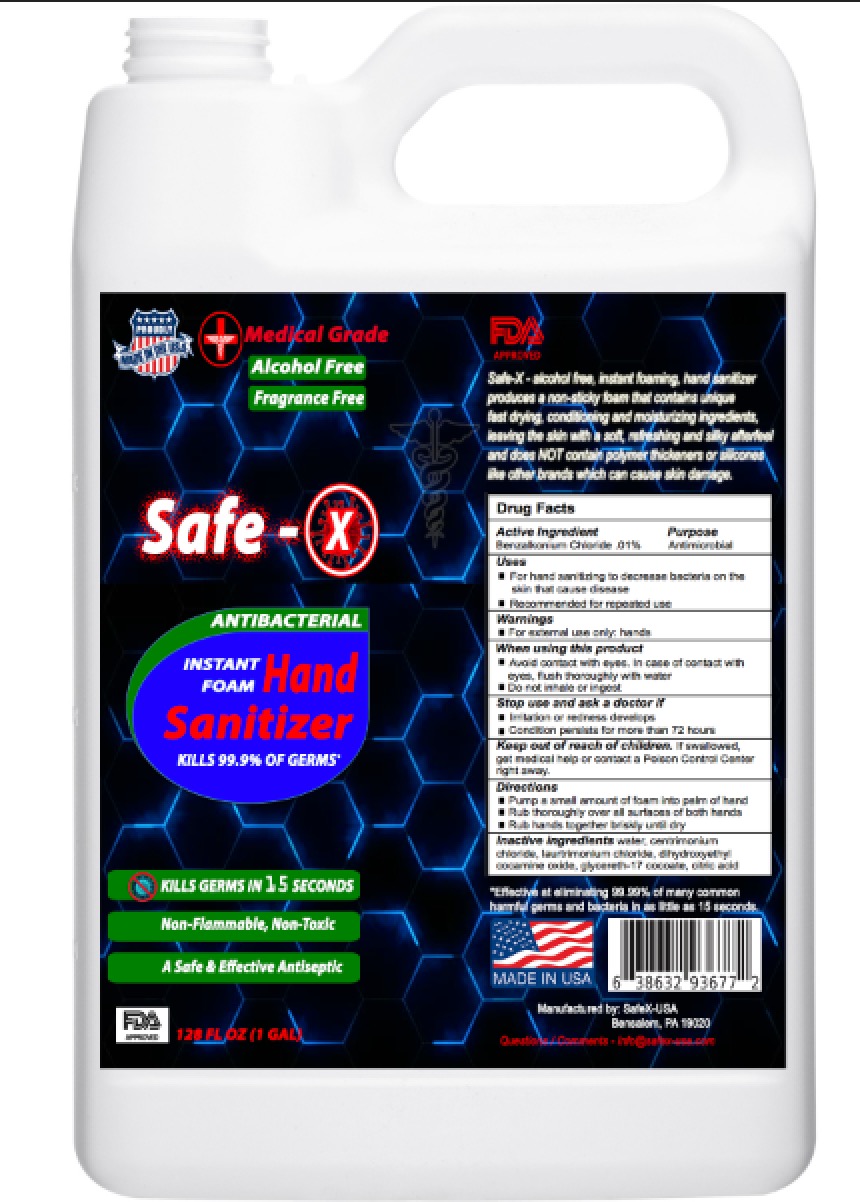 DRUG LABEL: Safe - X
NDC: 77164-618 | Form: LIQUID
Manufacturer: Green Smart Plastics LLC
Category: otc | Type: HUMAN OTC DRUG LABEL
Date: 20200618

ACTIVE INGREDIENTS: BENZALKONIUM CHLORIDE 0.13 mg/1 mL
INACTIVE INGREDIENTS: DIHYDROXYETHYL COCAMINE OXIDE; ANHYDROUS CITRIC ACID; WATER; CETRIMONIUM CHLORIDE; GLYCERETH-17 COCOATE; LAURTRIMONIUM CHLORIDE

Active Ingredient

Ask Doctor section

Keep out childern

Inactive Ingredien

WARNINGS

Warnign Section

Indication Usage

Dosage

Dosage & Admin

Purpose section

Package label